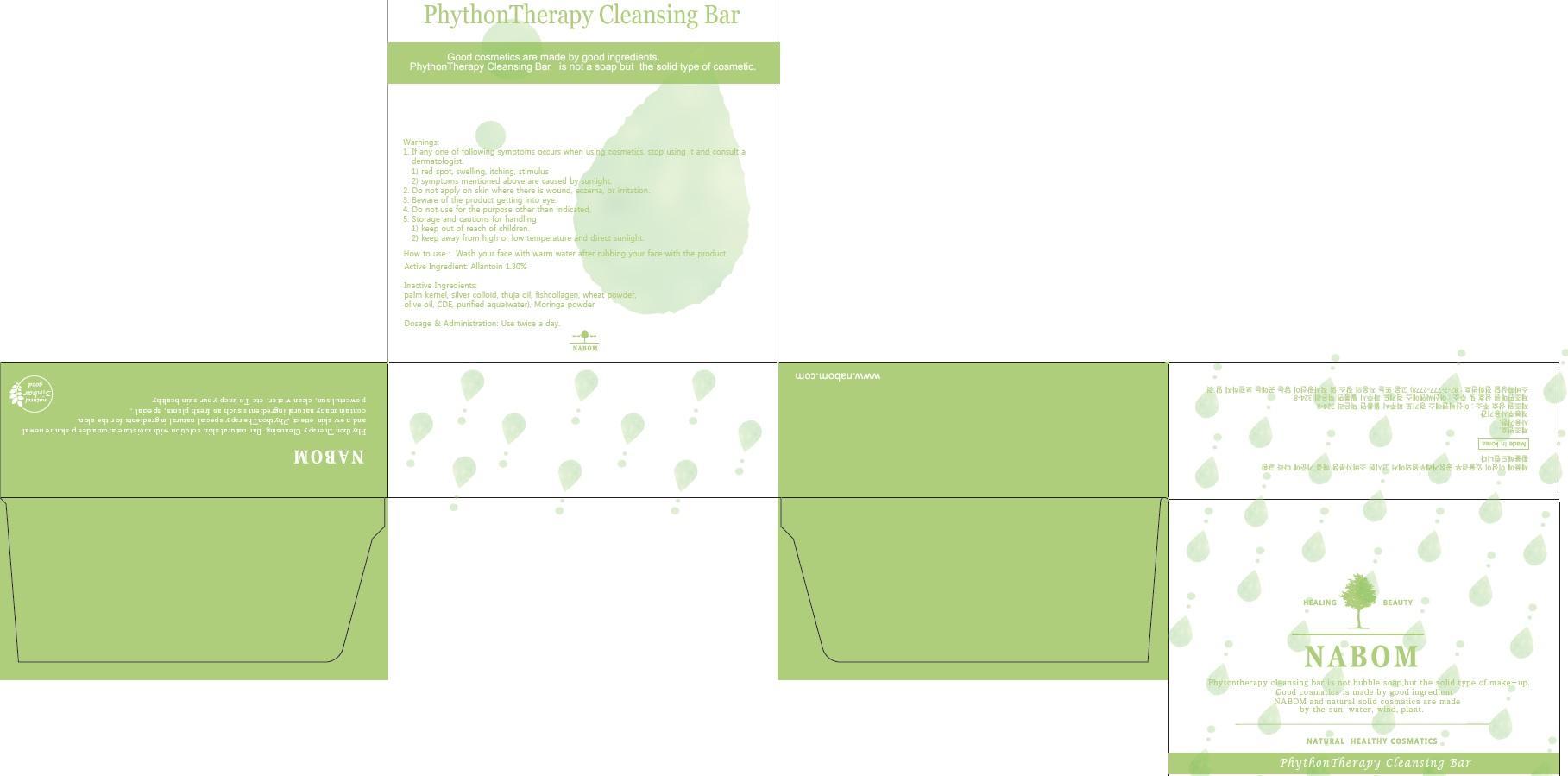 DRUG LABEL: PHYTON THERAPY CLEANSING BAR
NDC: 69694-010 | Form: SOAP
Manufacturer: Nature In
Category: otc | Type: HUMAN OTC DRUG LABEL
Date: 20150326

ACTIVE INGREDIENTS: Allantoin 1.30 g/100 g
INACTIVE INGREDIENTS: PALM KERNEL OIL

ACTIVE INGREDIENT

Active Ingredient: Allantoin 1.30%

INACTIVE INGREDIENT

Inactive Ingredients: palm kernel, silver colloid, thuja oil, fishcollagen, wheat powder, olive oil, CDE, purified aqua(water), Moringa powder

PURPOSE

Purpose: Skin Protectant

WARNINGS

Warnings: 1. If any one of following symptoms occurs when using cosmetics, stop using it and consult a dermatologist. 1) red spot, swelling, itching, stimulus 2) symptoms mentioned above are caused by sunlight. 2. Do not apply on skin where there is wound, eczema, or irritation. 3. Beware of the product getting into eye. 4. Do not use for the purpose other than indicated. 5. Storage and cautions for handling 1) keep out of reach of children. 2) keep away from high or low temperature and direct sunlight.

KEEP OUT OF REACH OF CHILDREN

INDICATIONS & USAGE

Indications & Usage: Wash your face with warm water after rubbing your face with the product.

DOSAGE & ADMINISTRATION

Dosage & Administration: Use twice a day.